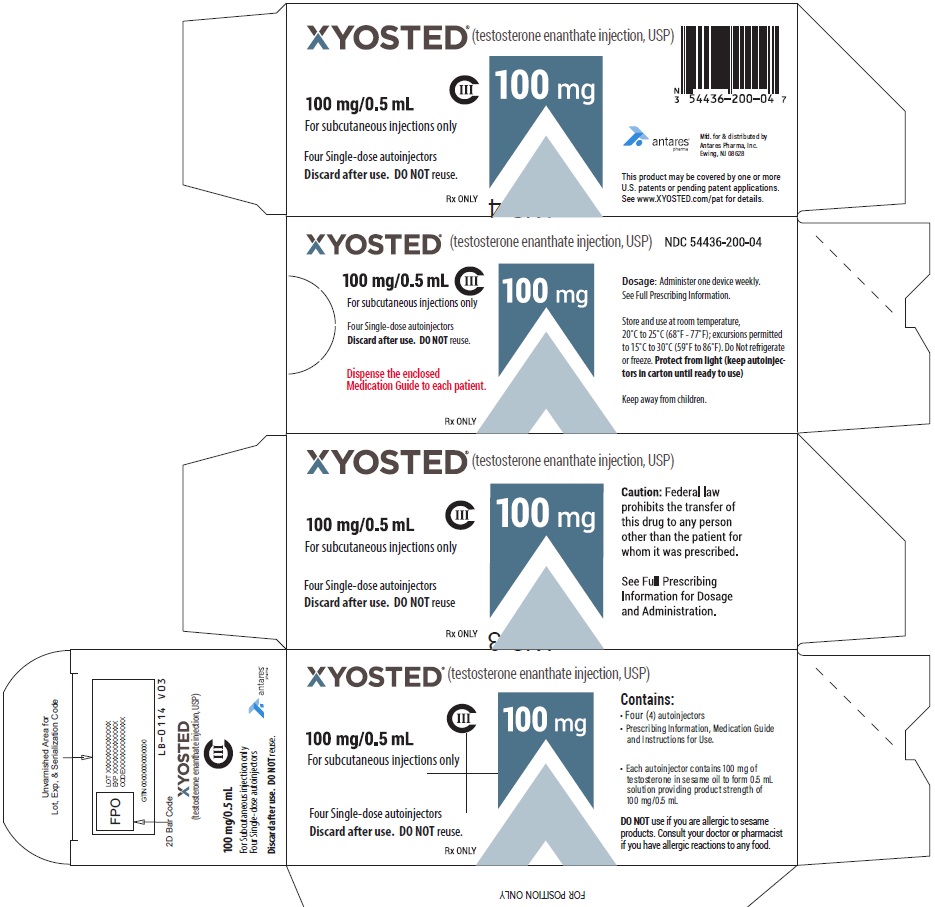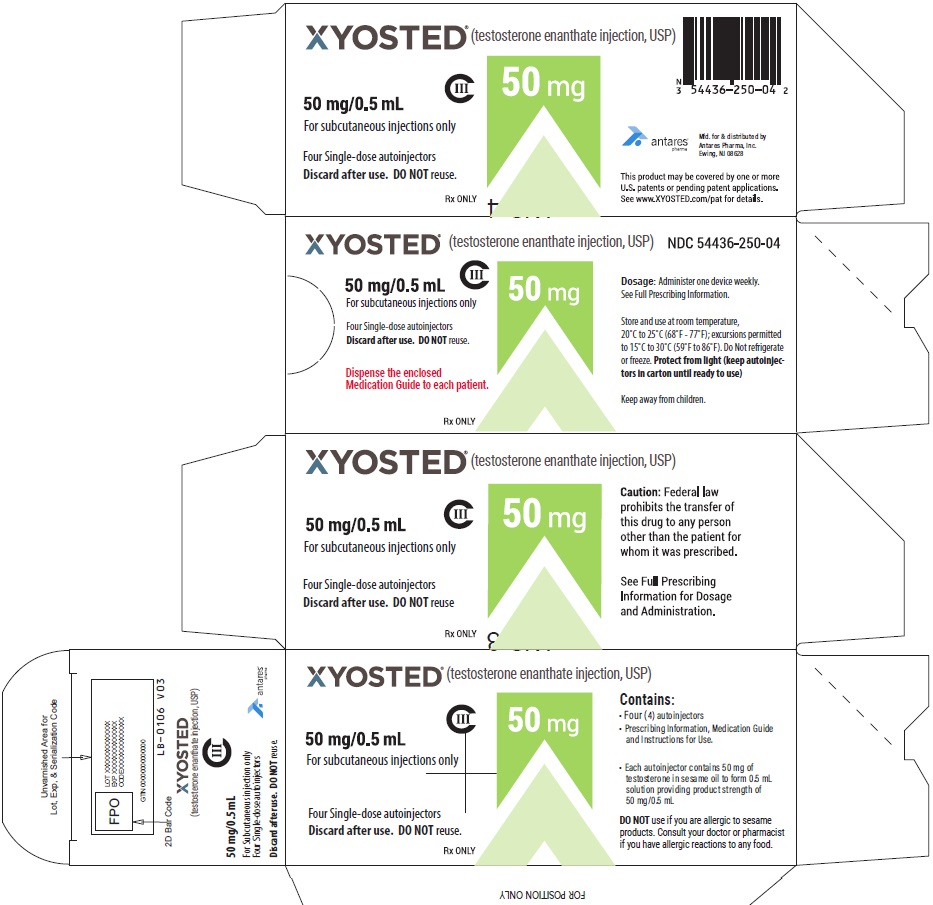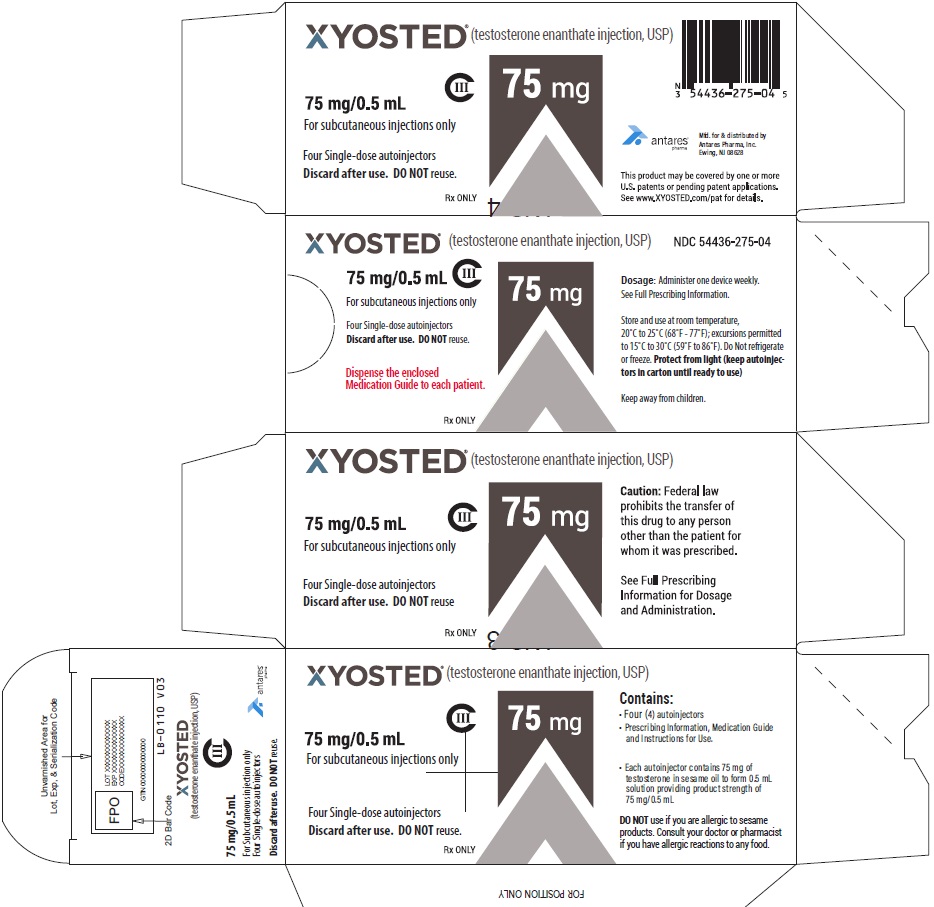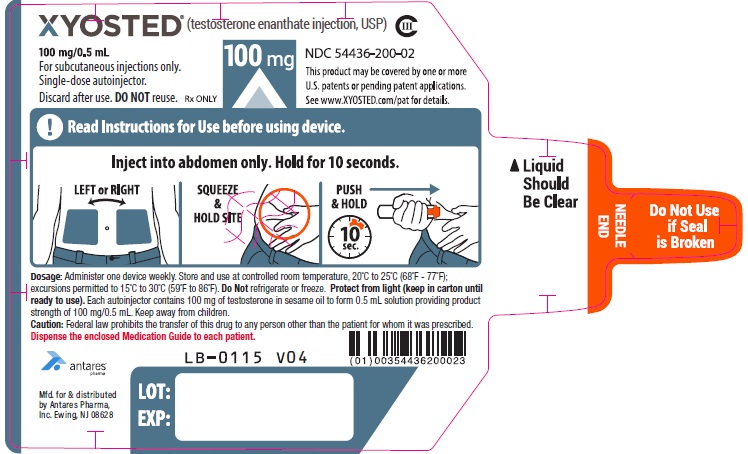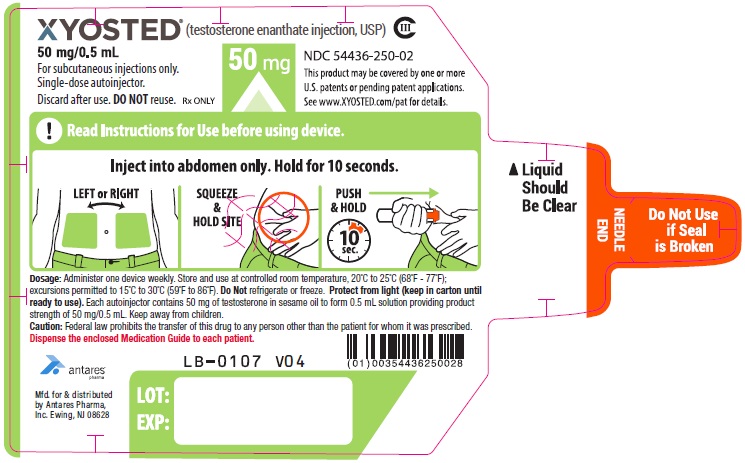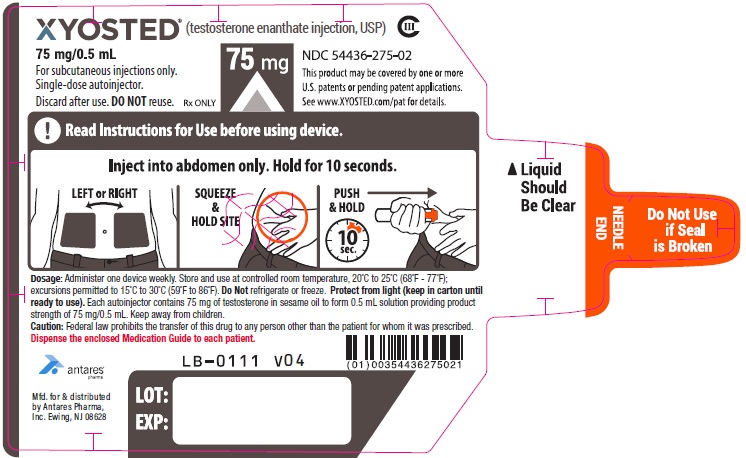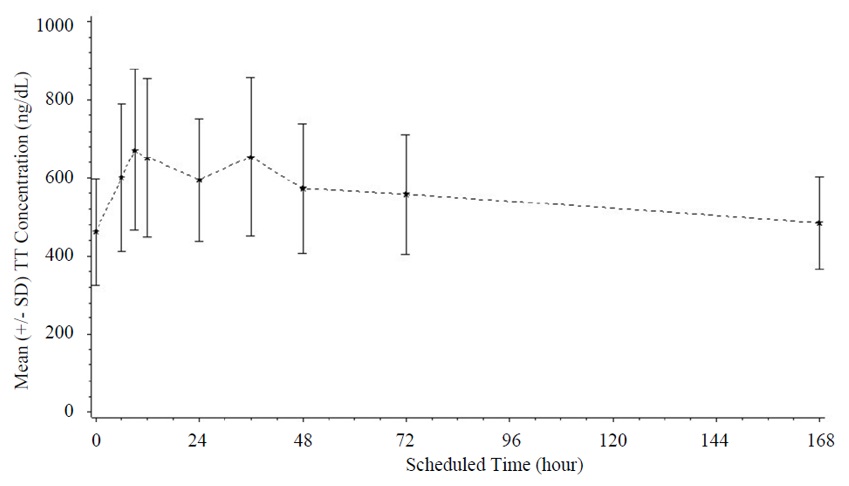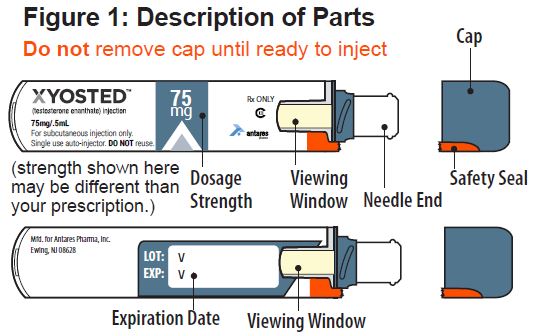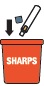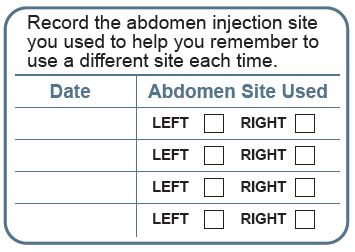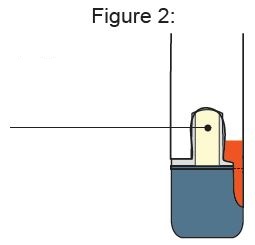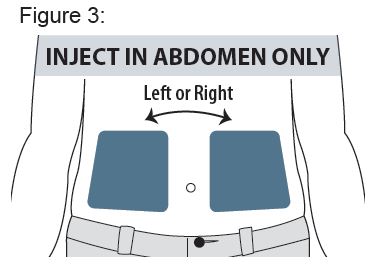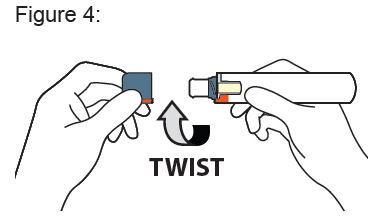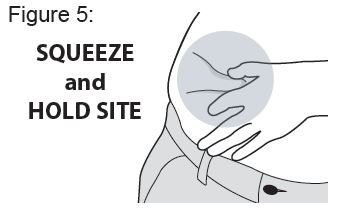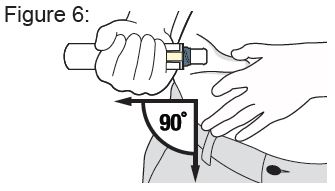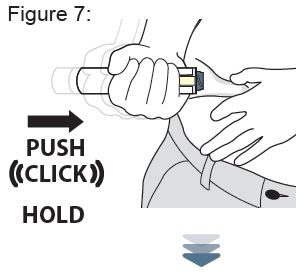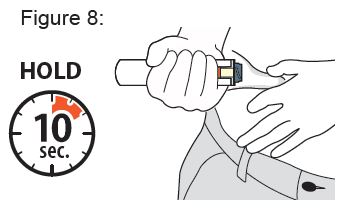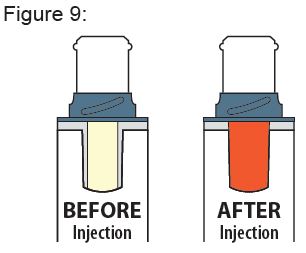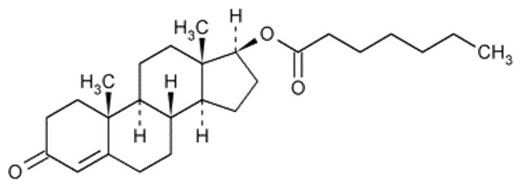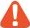 DRUG LABEL: XYOSTED
NDC: 54436-250 | Form: INJECTION
Manufacturer: Antares Pharma, Inc.
Category: prescription | Type: HUMAN PRESCRIPTION DRUG LABEL
Date: 20250722
DEA Schedule: CIII

ACTIVE INGREDIENTS: TESTOSTERONE ENANTHATE 50 mg/0.5 mL
INACTIVE INGREDIENTS: SESAME OIL

HIGHLIGHTS OF PRESCRIBING INFORMATION

These highlights do not include all the information needed to use XYOSTED® safely and effectively. See full prescribing information for XYOSTED.
XYOSTED (testosterone enanthate) injection, for subcutaneous use
CIII
Initial U.S. approval: 1953

RECENT MAJOR CHANGES

Boxed Warnings, Blood Pressure Increases | Removed 03/2025
Warnings and Precautions, Venous Thromboembolism (5.2) | 03/2025
Warnings and Precautions, Blood Pressure Increases (5.4) | 03/2025
Warnings and Precautions, Cardiovascular Risk (5.4) | Removed 03/2025

1 INDICATIONS AND USAGE

XYOSTED (testosterone enanthate) injection is an androgen indicated for testosterone replacement therapy in adult males for conditions associated with a deficiency or absence of endogenous testosterone (1).

Limitations of Use:

- Safety and efficacy of XYOSTED in men with “age-related hypogonadism” has not been established (1).
- Safety and efficacy of XYOSTED in males less than 18 years old have not been established (1, 8.4).

2 DOSAGE AND ADMINISTRATION

- Prior to initiating XYOSTED: confirm the diagnosis of hypogonadism by ensuring that serum testosterone has been measured in the morning on at least two separate days and that these concentrations are below the normal range (2.1).
- Starting dose: 75 mg subcutaneously in the abdominal region once weekly. Avoid intramuscular and intravascular administration (2.2, 2.3).
- Dose Adjustment: Based upon total testosterone trough concentrations (measured 7 days after most recent dose) obtained following 6 weeks of dosing and periodically thereafter (2.2).
- Discard unused portion (2.3)

3 DOSAGE FORMS AND STRENGTHS

- XYOSTED (testosterone enanthate) Injection is supplied as 0.5 mL of sterile solution in a single-dose autoinjector for subcutaneous administration in three strengths (3):
  - 50 mg/0.5 mL
  - 75 mg/0.5 mL
  - 100 mg/0.5 mL

4 CONTRAINDICATIONS

- Men with carcinoma of the breast or known or suspected carcinoma of the prostate (4, 5.4).
- Women who are pregnant (4, 8.1). Testosterone may cause fetal harm (4, 5.7, 8.1, and 8.2).
- Known hypersensitivity to XYOSTED or its ingredients (4).

5 WARNINGS AND PRECAUTIONS

- Polycythemia: Monitor hematocrit approximately every 3 months to detect increased red blood cell mass and polycythemia (5.1).
- Venous thromboembolism (VTE): VTE including deep vein thrombosis (DVT) and pulmonary embolism (PE), have been reported in patients using testosterone products. Evaluate patients with signs or symptoms consistent with DVT or PE (5.2).
- Worsening of Benign Prostatic Hyperplasia (BPH) and Potential Risk of Prostate Cancer: Monitor patients with BPH for worsening signs and symptoms of BPH (5.3).
- Blood Pressure Increases: Testosterone can increase blood pressure, which can increase cardiovascular risk over time. Measure blood pressure periodically. Not recommended for use in men with uncontrolled hypertension (5.4).
- Abuse of Testosterone: Testosterone has been subject to abuse, typically at doses higher than recommended for the approved indication and in combination with other anabolic androgenic steroids (5.5).
- Potential for Adverse Effects on Spermatogenesis: Exogenous administration of androgens may lead to azoospermia (5.7).
- Edema: Edema with or without congestive heart failure may be a complication in patients with preexisting cardiac, renal, or hepatic disease (5.9).
- Sleep apnea: Sleep apnea may occur in those with risk factors (5.11).
- Monitor prostatic specific antigen (PSA) and lipid concentrations periodically (5.3, 5.12).
- Depression and suicidal ideation and behavior, including completed suicide, have occurred during clinical trials in patients treated with XYOSTED (5.15).

6 ADVERSE REACTIONS

The most commonly reported adverse reactions (>5%) were: hematocrit increased, hypertension, PSA increased, injection site bruising, and headache. (6.1)

To report SUSPECTED ADVERSE REACTIONS, contact Antares at 1-844-XYOSTED (1-844-996-7833) or FDA at 1-800-FDA-1088 or www.fda.gov/medwatch.

7 DRUG INTERACTIONS

- Androgens may decrease blood glucose, and therefore may decrease insulin requirements in diabetic patients (7.1).
- Changes in anticoagulant activity may be seen with androgens. More frequent monitoring of international normalized ratio (INR) and prothrombin time is recommended in patients taking warfarin (7.2).
- Use of testosterone with corticosteroids may result in increased fluid retention. Use with caution, particularly in patients with cardiac, renal, or hepatic disease (7.3).
- Concomitant administration of medications that are known to increase BP with XYOSTED may lead to additional increases in BP (7.4).

8 USE IN SPECIFIC POPULATIONS

- Geriatric Patients: There are insufficient long-term safety data to assess the potential risks of cardiovascular disease and prostate cancer (8.5).

FULL PRESCRIBING INFORMATION

1 INDICATIONS AND USAGE

XYOSTED (testosterone enanthate) injection is an androgen indicated for testosterone replacement therapy in adult males for conditions associated with a deficiency or absence of endogenous testosterone.

- Primary hypogonadism (congenital or acquired): testicular failure due to cryptorchidism, bilateral torsion, orchitis, vanishing testis syndrome, orchiectomy, Klinefelter's syndrome, chemotherapy, or toxic damage from alcohol or heavy metals. These men usually have low serum testosterone concentrations and gonadotropins (follicle-stimulating hormone [FSH], luteinizing hormone [LH]) above the normal range.
- Hypogonadotropic hypogonadism (congenital or acquired): gonadotropin or luteinizing hormone-releasing hormone (LHRH) deficiency or pituitary-hypothalamic injury from tumors, trauma, or radiation. These men have low testosterone serum concentrations but have gonadotropins in the normal or low range.

Limitations of Use:

- Safety and efficacy of XYOSTED in men with “age-related hypogonadism” has not been established.
- Safety and efficacy of XYOSTED in males less than 18 years old have not been established [see Use in Specific Populations (8.4)].

2 DOSAGE AND ADMINISTRATION

2.1 Confirmation of Hypogonadism Before Initiation of XYOSTED

Prior to initiating XYOSTED, confirm the diagnosis of hypogonadism by ensuring that serum testosterone concentrations have been measured in the morning on at least two separate days and that these serum testosterone concentrations are below the normal range.

2.2 Starting Dose and Dose Adjustment

The starting dose of XYOSTED is 75 mg, administered subcutaneously in the abdominal region once a week.

Dose adjustment

Measure total testosterone trough concentrations (measured 7 days after the most recent dose) following 6 weeks of dosing, following 6 weeks after dose adjustment, and periodically while on treatment with XYOSTED. A trough concentration between 350 ng/dL and 650 ng/dL generally provides testosterone exposures in the normal range during the entire dosing interval.

Decrease the dose by 25 mg if the total testosterone trough concentration (Ctrough) is ≥650 ng/dL.
Increase the dose by 25 mg if the total testosterone Ctrough is <350 ng/dL.
Maintain the same dose if the total testosterone Ctrough is ≥350 ng/dL and <650 ng/dL.

2.3 Important Administration Instructions

XYOSTED is for subcutaneous injection in the abdominal region only. Avoid intramuscular or intravascular injection.

Instruct patients on the proper use of XYOSTED and direct them to use the proper injection site. Refer to the Instructions for Use for proper use of XYOSTED.

Visually inspect XYOSTED for particulate matter and discoloration prior to administration. Do not use if the liquid is cloudy or if visible particles are present.

Do not use XYOSTED if the seal is broken. Discard unused portion.

3 DOSAGE FORMS AND STRENGTHS

XYOSTED injection is available as 0.5 mL of a sterile, preservative-free and nonpyrogenic, clear, colorless to yellow solution containing testosterone enanthate. It is supplied in a single-dose syringe assembled in an autoinjector for subcutaneous administration. XYOSTED is available in three dosage strengths:

50 mg/0.5 mL

75 mg/0.5 mL

100 mg/0.5 mL

4 CONTRAINDICATIONS

XYOSTED is contraindicated in:

- Men with carcinoma of the breast or known or suspected carcinoma of the prostate [see Warnings and Precautions (5.4)].
- Women who are pregnant. Testosterone can cause virilization of the female fetus when administered to a pregnant woman [see Use in Specific Populations (8.1)].
- Men with known hypersensitivity to XYOSTED or any of its ingredients (testosterone enanthate and sesame oil).

5 WARNINGS AND PRECAUTIONS

5.1 Polycythemia

Increases in hematocrit reflective of increases in red blood cell mass may require discontinuation of XYOSTED.

Check that hematocrit is not elevated prior to initiating XYOSTED. Evaluate hematocrit approximately every 3 months while the patient is on XYOSTED. If hematocrit becomes elevated, stop XYOSTED until the hematocrit decreases to an acceptable level. If XYOSTED is restarted and again causes hematocrit to become elevated, stop XYOSTED permanently. An increase in red blood cell mass may increase the risk of thromboembolic events.

5.2 Venous Thromboembolism

There have been postmarketing reports of venous thromboembolic events, including deep vein thrombosis (DVT) and pulmonary embolism (PE), in patients using testosterone products, such as XYOSTED.

In the Testosterone Replacement therapy for Assessment of long-term Vascular Events and efficacy Response in hypogonadal men (TRAVERSE) Study, a randomized, double-blind, placebo-controlled, cardiovascular (CV) outcomes study, compared to placebo, topical testosterone gel was associated with a numerically higher incidence of VTE (1.7% vs 1.2%) which included DVT (0.6% vs 0.5%) and PE events (0.9% vs 0.5%) [see Adverse Reactions (6.1)].

Evaluate patients who report symptoms of pain, edema, warmth and erythema in the lower extremity for DVT and those who present with acute shortness of breath for PE. If a venous thromboembolic event is suspected, discontinue treatment with XYOSTED and initiate appropriate workup and management.

5.3 Worsening of Benign Prostatic Hyperplasia (BPH) and Potential Risk of Prostate Cancer

Patients with BPH treated with androgens are at an increased risk of worsening of signs and symptoms of BPH. Monitor patients with BPH for worsening signs and symptoms.

Patients treated with androgens may be at an increased risk for prostate cancer. Evaluate patients for prostate cancer prior to initiating and during treatment with androgens [see Contraindications (4)].

5.4 Blood Pressure Increases

XYOSTED can increase blood pressure. Ambulatory blood pressure monitoring (ABPM) demonstrated XYOSTED increased systolic/diastolic BP by an average of 3.9/1.5 mm Hg from baseline after 12 weeks of treatment in clinical trials [see Adverse Reactions (6.1)]. In patients with hypertension on antihypertensive therapy, XYOSTED increased the mean systolic/diastolic BP by 3.9/1.3 mm Hg from baseline.

The CV risk associated with topical testosterone gel was evaluated in TRAVERSE, a randomized, double-blind, placebo-controlled, CV outcomes study in men with a history of CV disease or multiple CV risk factors. In TRAVERSE, topical testosterone gel increased mean systolic blood pressure by 1.0 mm Hg from baseline to 36 months, whereas a mean decrease from baseline of 0.5 mm Hg was observed in the placebo group at this timepoint, for a mean between-group difference of 1.5 mm Hg. However, the incidences of major adverse cardiovascular events (MACE), including cardiovascular death, nonfatal myocardial infarction [MI] and non-fatal stroke, were similar between treatment groups (7% for topical testosterone gel vs 7.3% for placebo) [See Adverse Reactions (6.1)].

Monitor blood pressure periodically in men using XYOSTED, especially men with hypertension. XYOSTED is not recommended for use in patients with uncontrolled hypertension.

5.5 Abuse of Testosterone and Monitoring of Serum Testosterone Concentrations

Testosterone has been subject to abuse, typically at doses higher than recommended for the approved indication and in combination with other anabolic androgenic steroids. Anabolic androgenic steroid abuse can lead to serious cardiovascular and psychiatric adverse reactions [see Drug Abuse and Dependence (9)].

If testosterone abuse is suspected, check serum testosterone concentrations to ensure they are within therapeutic range. However, testosterone levels may be in the normal or subnormal range in men abusing synthetic testosterone derivatives. Counsel patients concerning the serious adverse reactions associated with abuse of testosterone and anabolic androgenic steroids. Conversely, consider the possibility of testosterone and anabolic androgenic steroid abuse in suspected patients who present with serious cardiovascular or psychiatric adverse events.

5.6 Not for Use in Women

Due to lack of controlled studies in women and potential virilizing effects, XYOSTED is not indicated for use in women [see Contraindications (4) and Use in Specific Populations (8.1, 8.2)].

5.7 Potential for Adverse Effects on Spermatogenesis

With large doses of exogenous androgens, including XYOSTED, spermatogenesis may be suppressed through feedback inhibition of pituitary follicle-stimulating hormone (FSH) which could possibly lead to adverse effects on semen parameters including sperm count [see Use in Specific Populations (8.3)]. Patients should be informed of this possible risk when deciding whether to use or to continue to use XYOSTED.

5.8 Hepatic Adverse Effects

Prolonged use of high doses of orally active 17-alpha-alkyl androgens (e.g., methyltestosterone) has been associated with serious hepatic adverse effects (peliosis hepatis, hepatic neoplasms, cholestatic hepatitis, and jaundice). Peliosis hepatis can be a life-threatening or fatal complication. Long-term therapy with intramuscular testosterone enanthate, which elevates blood levels for prolonged periods, has produced multiple hepatic adenomas. XYOSTED is not known to produce these adverse effects. Nonetheless, patients should be instructed to report any signs or symptoms of hepatic dysfunction (e.g., jaundice). If these occur, promptly discontinue XYOSTED while the cause is evaluated.

5.9 Edema

Androgens, including XYOSTED, may promote retention of sodium and water. Edema with or without congestive heart failure may be a serious complication in patients with preexisting cardiac, renal, or hepatic disease. In addition to discontinuation of the drug, diuretic therapy may be required.

5.10 Gynecomastia

Gynecomastia may develop and may persist in patients being treated for hypogonadism.

5.11 Sleep Apnea

Treatment with testosterone products including XYOSTED may potentiate sleep apnea in some patients, especially those with risk factors such as obesity or chronic lung disease.

5.12 Lipid Changes

Changes in the serum lipid profile may require dose adjustment of lipid lowering drugs or discontinuation of testosterone therapy. Monitor the lipid profile periodically, particularly after starting testosterone therapy.

5.13 Hypercalcemia

Androgens, including XYOSTED, should be used with caution in cancer patients at risk of hypercalcemia (and associated hypercalciuria). Monitor serum calcium concentrations regularly during treatment with XYOSTED in these patients.

5.14 Decreased Thyroxine-binding Globulin

Androgens, including XYOSTED, may decrease concentrations of thyroxine-binding globulin, resulting in decreased total T4 serum concentrations and increased resin uptake of T3 and T4. Free thyroid hormone concentrations remain unchanged, however, and there is no clinical evidence of thyroid dysfunction.

5.15 Risk of Depression and Suicide

Depression and suicidal ideation and behavior, including completed suicide, have occurred during clinical trials in patients treated with XYOSTED. Advise patients and caregivers to seek medical attention for manifestations of suicidal ideation or behavior, new onset or worsening depression, anxiety, or other mood changes.

6 ADVERSE REACTIONS

6.1 Clinical Trials Experience

Because clinical trials are conducted under widely varying conditions, adverse reaction rates observed in the clinical trials of a drug cannot be directly compared with rates in the clinical trials of another drug and may not reflect the rates observed in practice.

The safety of XYOSTED was evaluated in 2 clinical studies in a total of 283 men who received weekly subcutaneous doses for up to one year. All patients were started on 75 mg weekly, then the dose was titrated to 50 mg or 100 mg weekly, as needed, to achieve pre-dose total testosterone concentrations of ≥350 ng/dL and <650 ng/dL.

Table 1 summarizes adverse reactions (≥2%) reported in a one-year study with XYOSTED.

Table 1. Number (%) of Patients with Adverse Reactions ≥2% in a 1 Year study with XYOSTED

Preferred Term | Overall (N=150); n (%)
Hematocrit increased | 21 (14.0)
Hypertension | 19 (12.7)
Prostatic specific antigen (PSA) increased | 18 (12.0)
Injection site bruising | 10 (6.7)
Headache | 8 (5.3)
Back pain | 5 (3.3)
Blood creatine phosphokinase increased | 5 (3.3)
Injection site hemorrhage | 5 (3.3)
Acne | 4 (2.7)
Blood testosterone increased | 4 (2.7)
Cough | 4 (2.7)
Edema peripheral | 4 (2.7)
Injection site erythema | 4 (2.7)
Prostatitis | 4 (2.7)
Urinary tract infection | 4 (2.7)
Abdominal pain | 3 (2.0)
Arthralgia | 3 (2.0)
Fatigue | 3 (2.0)
Hematuria | 3 (2.0)
Polycythemia | 3 (2.0)
Sleep apnea syndrome | 3 (2.0)
Note: Includes events that started on or after the first dosing, or existed prior to the first dose and worsened in severity or relatedness after dosing. Percentage was calculated using the number of patients in the column heading as the denominator.

Table 2 summarizes the adverse reactions (≥2%) reported in a 6-month study with XYOSTED.

Table 2. Number (%) of Patients with Adverse Reactions ≥2% in a 6-Month Study with XYOSTED

Preferred Term | Overall (N = 133); n (%)
Hematocrit increased | 11 (8.3)
Injection site hemorrhage | 8 (6.0)
Blood creatine phosphokinase increased | 5 (3.8)
Injection site bruising | 5 (3.8)
Prostatitis | 4 (3.0)
Prostatic specific antigen (PSA) increased | 4 (3.0)
Urinary tract infection | 4 (3.0)
Fatigue | 3 (2.3)
Hypertension | 3 (2.3)
Insomnia | 3 (2.3)
Nausea | 3 (2.3)
Note: Includes events that started on or after the first dosing, or existed prior to the first dose and worsened in severity or relatedness after dosing. Percentage was calculated using the number of patients in the column heading as the denominator.

BP Increases in the 6-Month Clinical Study

In the 6-month clinical study, 24-hour ambulatory blood pressure monitoring (ABPM) was conducted in 133 patients, 113 of whom completed the study. ABPM was conducted at 3 distinct 24-hour time periods: at Baseline and following 6 and 12 weeks of XYOSTED therapy. A total of 62 patients had acceptable ABPM recordings at baseline and Week 12. In that group, the mean change in systolic and diastolic BP from baseline to Week 12 was + 3.9 mm Hg (95% CI 1.4-6.4) and + 1.5 mm Hg (95% CI 0.4-2.6), respectively. In patients with a history of hypertension who were receiving antihypertensive therapy, the mean ABPM systolic and diastolic BP increased by +3.9 mm Hg [95% CI 0.19-7.7] and +1.3 mm Hg [95% CI -0.37-3.0], respectively [n=33]). In patients with no history of hypertension, the mean ABPM systolic and diastolic blood pressure increased by +4.1 mm Hg [95% CI 0.43-7.8] and +1.9 mm Hg [95% CI 0.055-3.7], respectively [n=28]).

10% of XYOSTED-treated patients were either started on antihypertensive medications or required changes to their antihypertensive medication regimen during the 1-year study.

A total of 3 patients were reported to have an adverse reaction of hypertension (2 patients with hypertension and 1 patient with worsening hypertension), and 1 was reported to have an adverse reaction of increased blood pressure.

Increases in Hematocrit

Increases in hematocrit to ≥55% were reported for 12 of the 283 patients in the 2 clinical studies, representing 4.2% of patients who received XYOSTED for up to one year. While the studies did not pre-define clinical adverse events related to increased hematocrit, polycythemia was reported as a medically significant adverse event in the investigator’s clinical judgment in 1.8% of treated patients. XYOSTED dosing resulted in mean hemoglobin increases of 1.0 ± 1.1 g/dL at 6 months and 1.1 ± 1.4 g/dL at 1 year and mean hematocrit increases of 3.8 ± 3.4% at 6 months and 5.4 ± 3.4% at 1 year.

Injection Site Reactions

Injection site reactions, including injection site bruising, injection site hemorrhage, injection site erythema and injection site induration were reported in 36 of the 283 patients in the 2 clinical studies, representing 12.7% of patients who received XYOSTED for up to one year. No patients discontinued XYOSTED because of injection site reactions.

Depression and Suicide Attempts

Depression requiring discontinuation was reported in 2 of the 283 patients in the two clinical studies and suicide attempts (one complete and one incomplete) were reported in 2 additional patients, comprising a total of 4 patients, representing 1.4% of patients who received XYOSTED for up to one year.

Increases in Serum PSA

Increases in serum PSA concentrations, defined as an increase from baseline of at least 1.4 ng/mL, or PSA greater than 4 ng/mL, led to discontinuation in 4.6% of the 283 patients in the 2 clinical studies.

Cardiovascular Outcomes

TRAVERSE was a randomized, double-blind, cardiovascular outcomes study to assess the cardiovascular (CV) safety of topical testosterone gel compared to placebo in 5198 hypogonadal men aged 45 to 80 years with a history of CV disease or with multiple CV risk factors. The primary outcome was the incidence of the composite endpoint of major adverse cardiovascular events (MACE), consisting of CV death, non-fatal myocardial infarction (MI), and non-fatal stroke.

The mean duration of therapy was approximately 22 months. The mean duration of follow-up was 33 months. Approximately 61% of all patients discontinued topical testosterone gel or placebo therapy.

The mean patient age (±SD) was 63.3 (7.9) years, with 2452 patients aged 65 years or more (47%); 2847 (about 55%) patients had pre-existing cardiovascular disease, whereas 2357 patients (about 45%) had an elevated cardiovascular risk at baseline, and mean BMI was 35 kg/m^2. Approximately 80% of patients were White, 17% were Black, and 3% were of other races or ethnic groups. Approximately 69%, 84%, and 93% had diabetes mellitus, hyperlipidemia, and hypertension, respectively.

The mean serum testosterone concentration at baseline in patients receiving topical testosterone gel was 220.4 ng/dL (n=2596). The mean serum testosterone concentrations at 12 months, 24 months, 36 months, and 48 months in patients receiving topical testosterone gel were 440.5 ng/dL (n=1683), 420.9 ng/dl (n=1125), 428.7 ng/dL (n=731), and 365.2 ng/dL (n=220), respectively.

For patients treated with topical testosterone gel, the incidence of MACE was 7.0% (n=182 events) and for those receiving placebo, the incidence of MACE was 7.3% (n=190 events). The study demonstrated noninferiority of topical testosterone gel versus placebo because the upper bound of 95% CI was less than the prespecified risk margin, of 1.5 for MACE (Hazard Ratio 0.96 [95% CI: 0.78, 1.17]).

Additional Adverse Reactions Reported in TRAVERSE

Additional adverse reactions reported in TRAVERSE at an incidence rate >2% in either treatment group and greater in topical testosterone gel versus placebo included: nonfatal arrythmias warranting intervention (5.2% vs 3.3%), atrial fibrillation (3.5% vs 2.4%), acute kidney injury (2.3% vs 1.5%) and bone fracture (3.5% vs 2.5%). For the adverse reaction of bone fracture, each event was adjudicated by clinical review.

7 DRUG INTERACTIONS

7.1 Insulin

Changes in insulin sensitivity or glycemic control may occur in patients treated with androgens. In diabetic patients, the metabolic effects of androgens may decrease blood glucose and, therefore, may necessitate a decrease in the dose of anti-diabetic medication.

7.2 Oral Anticoagulants

Changes in anticoagulant activity may be seen with androgens, therefore more frequent monitoring of international normalized ratio (INR) and prothrombin time are recommended in patients taking warfarin, especially at the initiation and termination of androgen therapy.

7.3 Corticosteroids

The concurrent use of testosterone with corticosteroids may result in increased fluid retention and requires careful monitoring, particularly in patients with cardiac, renal or hepatic disease.

7.4 Medications that May Also Increase Blood Pressure

Some prescription medications and nonprescription analgesic and cold medications contain drugs known to increase blood pressure. Concomitant administration of these medications with XYOSTED may lead to additional increases in blood pressure.

8 USE IN SPECIFIC POPULATIONS

8.1 Pregnancy

Risk Summary

XYOSTED is contraindicated in pregnant women. Testosterone is teratogenic and may cause fetal harm when administered to a pregnant woman based on data from animal studies and its mechanism of action [see Contraindications (4) and Clinical Pharmacology (12.1)]. Exposure of a female fetus to androgens may result in varying degrees of virilization. In animal developmental studies, exposure to testosterone in utero resulted in hormonal and behavioral changes in offspring and structural impairments of reproductive tissues in female and male offspring. These studies did not meet current standards for nonclinical development toxicity studies.

Data
Animal Data

In developmental studies conducted in rats, rabbits, pigs, sheep and rhesus monkeys, pregnant animals received intramuscular injection of testosterone during the period of organogenesis. Testosterone treatment at doses that were comparable to those used for testosterone replacement therapy resulted in structural impairments in both female and male offspring. Structural impairments observed in females included increased ano-genital distance, phallus development, empty scrotum, no external vagina, intrauterine growth retardation, reduced ovarian reserve, and increased ovarian follicular recruitment. Structural impairments seen in male offspring included increased testicular weight, larger seminal tubular lumen diameter, and higher frequency of occluded tubule lumen. Increased pituitary weight was seen in both sexes.

Testosterone exposure in utero also resulted in hormonal and behavioral changes in offspring. Hypertension was observed in pregnant females and offspring in rats exposed to doses approximately twice those used for testosterone replacement therapy.

8.2 Lactation

Risk Summary

XYOSTED is not indicated for use in females.

8.3 Females and Males of Reproductive Potential

Infertility

During treatment with large doses of exogenous androgens, including XYOSTED, spermatogenesis may be suppressed through feedback inhibition of the hypothalamic-pituitary-testicular axis [see Warnings and Precautions (5.8)]. Reduced fertility is observed in some men taking testosterone replacement therapy. The impact on fertility may be irreversible.

8.4 Pediatric Use

Safety and effectiveness of XYOSTED in pediatric patients less than 18 years old have not been established. Improper use may result in acceleration of bone age and premature closure of epiphyses.

8.5 Geriatric Use

There have not been sufficient numbers of geriatric patients in controlled clinical studies with XYOSTED to determine whether efficacy or safety in those over 65 years of age differs from younger subjects. Of the 283 patients enrolled in the 6-month and one-year efficacy and safety clinical study utilizing XYOSTED, 49 (17%) were over 65 years of age. Additionally, there are insufficient long-term safety data in geriatric patients to assess the potentially increased risk of cardiovascular disease and prostate cancer.

Geriatric patients treated with androgens may also be at risk for worsening of signs and symptoms of BPH [see Warnings and Precautions (5.4)].

9. DRUG ABUSE AND DEPENDENCE

9.1 Controlled Substance

XYOSTED contains testosterone, a Schedule III controlled substance in the Controlled Substances Act.

9.2 Abuse

Drug abuse is intentional non-therapeutic use of a drug, even once, for its rewarding psychological and physiological effects. Abuse and misuse of testosterone are seen in male and female adults and adolescents. Testosterone, often in combination with other anabolic androgenic steroids (AAS), and not obtained by prescription through a pharmacy, may be abused by athletes and bodybuilders. There have been reports of misuse of men taking higher doses of legally obtained testosterone than prescribed and continuing testosterone despite adverse events or against medical advice.

Abuse-Related Adverse Reactions

Serious adverse reactions have been reported in individuals who abuse anabolic androgenic steroids, and include cardiac arrest, myocardial infarction, hypertrophic cardiomyopathy, congestive heart failure, cerebrovascular accident, hepatotoxicity, and serious psychiatric manifestations, including major depression, mania, paranoia, psychosis, delusions, hallucinations, hostility and aggression.

The following adverse reactions have also been reported in men: transient ischemic attacks, convulsions, hypomania, irritability, dyslipidemias, testicular atrophy, subfertility, and infertility.

The following additional adverse reactions have been reported in women: hirsutism, virilization, deepening of voice, clitoral enlargement, breast atrophy, male-pattern baldness, and menstrual irregularities.

The following adverse reactions have been reported in male and female adolescents: premature closure of bony epiphyses with termination of growth, and precocious puberty.

Because these reactions are reported voluntarily from a population of uncertain size and may include abuse of other agents, it is not always possible to reliably estimate their frequency or establish a causal relationship to drug exposure.

9.3 Dependence

Behaviors Associated with Addiction

Continued abuse of testosterone and other anabolic steroids, leading to addiction is characterized by the following behaviors:

- Taking greater doses than prescribed
- Continued drug use despite medical and social problems due to drug use
- Spending significant time to obtain the drug when supplies of the drug are interrupted
- Giving a higher priority to drug use than other obligations
- Having difficulty in discontinuing the drug despite desires and attempts to do so
- Experiencing withdrawal symptoms upon abrupt discontinuation of use

Physical dependence is characterized by withdrawal symptoms after abrupt drug discontinuation or a significant dose reduction of a drug. Individuals taking supratherapeutic doses of testosterone may experience withdrawal symptoms lasting for weeks or months which include depressed mood, major depression, fatigue, craving, restlessness, irritability, anorexia, insomnia, decreased libido and hypogonadotropic hypogonadism.

Drug dependence in individuals using approved doses of testosterone for approved indications has not been documented.

10 OVERDOSAGE

There have been no reports of overdosage in the XYOSTED clinical trials. There is a single report of acute overdosage with use of an approved injectable testosterone product. This subject had serum testosterone concentrations of up to 11,400 ng/dL, which were implicated in a cerebrovascular accident.

Treatment of overdosage consists of discontinuation of XYOSTED together with appropriate symptomatic and supportive care.

11 DESCRIPTION

XYOSTED (testosterone enanthate) injection contains testosterone enanthate, an ester derivative of an endogenous androgen, testosterone. Testosterone enanthate is a white to creamy white crystalline powder described by the chemical name (17β)-17-[(1-Oxoheptyl) oxy]-androst-4-en-3-one. Testosterone enanthate has the molecular formula C26H40O3, the molecular weight 400.59, and the molecular structure with the chemical formula:

XYOSTED (testosterone enanthate) injection is a sterile, preservative-free, and nonpyrogenic colorless to pale yellow solution supplied in a single-dose syringe assembled in a pressure-assisted autoinjector for subcutaneous administration. Each XYOSTED autoinjector contains 50 mg, 75 mg, or 100 mg of testosterone in sesame oil to form 0.5 mL solution providing three product strengths of 50 mg/0.5 mL, 75 mg/0.5 mL, and 100 mg/0.5 mL.

12 CLINICAL PHARMACOLOGY

12.1 Mechanism of Action

Endogenous androgens, including testosterone and dihydrotestosterone (DHT) are responsible for the normal growth and development of the male sex organs and for maintenance of secondary sex characteristics. These effects include the growth and maturation of the prostate, seminal vesicles, penis, and scrotum; the development of male hair distribution, such as facial, pubic, chest, and axillary hair; laryngeal enlargement, vocal cord thickening, and alterations in body musculature and fat distribution.

Male hypogonadism, a clinical syndrome resulting from insufficient secretion of testosterone, has two main etiologies. Primary hypogonadism is caused by defects of the gonads, such as Klinefelter’s syndrome or Leydig cell aplasia, whereas secondary hypogonadism is the failure of the hypothalamus (or pituitary) to produce sufficient gonadotropins (FSH, LH).

12.2 Pharmacodynamics

No specific pharmacodynamic studies were conducted using XYOSTED.

12.3 Pharmacokinetics

Absorption and Bioavailability

XYOSTED delivers physiologic amounts of testosterone, producing circulating testosterone concentrations that approximate normal concentrations (300-1100 ng/dL) seen in healthy men.

Following weekly subcutaneous injection of XYOSTED for 12 weeks, serum testosterone concentrations reached a maximum after a median of 11.9 hours post-dose (range: 5.8-168.7 hours) then slowly declined (Figure 1). In this study, the starting dose of XYOSTED was 75 mg weekly then the XYOSTED dose was adjusted based upon total testosterone trough concentrations obtained following 6 weeks of dosing [see Dosage and Administration (2.2)]. Steady state serum testosterone concentration was achieved by Week 6.

Figure 1. Mean (±SD) of Total Testosterone (TT) Concentration (ng/dL) Following Weekly Administration of XYOSTED for 12 Weeks (N=137)

At Week 12, total testosterone concentrations were measured before and at specified times up to 168 hours after XYOSTED administration then analyzed for pharmacokinetic (PK) parameters (Table 3).

Table 3. Arithmetic Mean (SD) and Range for Total Testosterone Pharmacokinetic Parameters at Week 12 Following Weekly Administration of 50 mg, 75 mg, or 100 mg XYOSTED (N=137)

 | Cavg (0-168 hr); (ng/dL) | Cmax; (ng/dL) | Tmax; (hr)a | Cmin; (ng/dL) | AUC (0-168 hr); (ng·hr/dL)
Mean (SD) | 553 (127) | 790 (215) | 11.9 | 436 (109) | 92,955 (21,385)
Min - Max | 276 - 1036 | 389 - 1410 | 6 - 168 | 166 - 788 | 46432 - 173,987

a Reported as median

Distribution

Circulating testosterone is primarily bound in serum to sex hormone-binding globulin (SHBG) and albumin. Approximately 40% of testosterone in plasma is bound to SHBG, 2% remains unbound (free), and the rest is loosely bound to albumin and other proteins.

Elimination

Metabolism

Testosterone enanthate is metabolized to testosterone via ester cleavage of the enanthate group. The mean (SD) maximum concentration of testosterone enanthate was 169 (68) ng/dL at Week 12 following weekly administration of XYOSTED.

Testosterone is metabolized to various 17-keto steroids through two different pathways. The major active metabolites of testosterone are estradiol and dihydrotestosterone (DHT). At pre-dose of Week 12 treatment, the mean DHT/testosterone ratio was 0.07 which was within the normal range.

Excretion

About 90% of a testosterone dose given intramuscularly is excreted in the urine as glucuronic and sulfuric acid-conjugates of testosterone or as metabolites. About 6% of a dose is excreted in the feces, mostly in the unconjugated form. Inactivation of testosterone occurs primarily in the liver.

13 NONCLINICAL TOXICOLOGY

13.1 Carcinogenesis, Mutagenesis, Impairment of Fertility

Carcinogenicity

Testosterone has been tested by subcutaneous injection and implantation in mice and rats. In mice, the implant induced cervical-uterine tumors, which metastasized in some cases. There is suggestive evidence that injection of testosterone into some strains of female mice increases their susceptibility to hepatoma. Testosterone is also known to increase the number of tumors and decrease the degree of differentiation of chemically induced carcinomas of the liver in rats.

Mutagenicity

Testosterone was negative in the in vitro Ames and in the in vivo mouse micronucleus assays.

Impairment of Fertility

The administration of exogenous testosterone suppresses spermatogenesis in the rat, dog and non-human primates, which was reversible on cessation of the treatment.

14 CLINICAL STUDIES

XYOSTED was evaluated in a 52-week, open-label study (NCT02159469) to evaluate its efficacy and safety when administered subcutaneously once weekly to 150 adult males with hypogonadism. The study included a Screening Phase, a Treatment Titration Phase, and an Extended Treatment Phase.

Patients were trained on proper use of XYOSTED to self-administer the initial dose of 75 mg once weekly on the same day of the week and at approximately the same time (7:00 am ± 2 hours). The dose was increased by 25 mg at Week 7 if the Week 6 serum total testosterone concentration at the end of the dosing interval (Ctrough) was <350 ng/dL, and was decreased by 25 mg if the Ctrough was ≥650 ng/dL.

The primary endpoint was the percentage of patients with a time-averaged serum total testosterone concentration (Cavg) over the 7-day dosing interval (0 to 168 hours) within the normal range (300 to 1100 ng/dL) at Week 12.

Secondary endpoints were the percentage of patients with a maximum total testosterone concentration (Cmax) above three predetermined limits: greater than 1500 ng/dL, between 1800 and 2500 ng/dL, and greater than 2500 ng/dL.

One hundred and thirty five (90%) of the 150 hypogonadal men who received XYOSTED had a serum total testosterone concentration Cavg(0-168h) within the normal range (300 to 1100 ng/dL) at Week 12. There were no patients (0%) with Cmax >1500 ng/dL at Week 12.

16 HOW SUPPLIED/STORAGE AND HANDLING

16.1 How Supplied

XYOSTED (testosterone enanthate) injection is provided as 0.5 mL of a sterile, preservative-free, and nonpyrogenic colorless to pale yellow solution in a single-dose syringe pre-assembled in an autoinjector for a single subcutaneous administration. XYOSTED is packaged in cartons containing four (4) or one (1) autoinjectors. XYOSTED is available in the following strengths and configurations.

- XYOSTED (testosterone enanthate) injection, USP, 50 mg/0.5 mL
  - Carton of 4 autoinjectors NDC 54436-250-04
  - Autoinjector NDC 54436-250-02
- XYOSTED (testosterone enanthate) injection, USP, 75 mg/0.5 mL
  - Carton of 4 autoinjectors NDC 54436-275-04
  - Carton of 1 autoinjector NDC 54436-275-05
  - Autoinjector NDC 54436-275-02
- XYOSTED (testosterone enanthate) injection, USP, 100 mg/0.5 mL
  - Carton of 4 autoinjectors NDC 54436-200-04
  - Carton of 1 autoinjector NDC 54436-200-05
  - Autoinjector NDC 54436-200-02

Before use, each autoinjector should be visually inspected. XYOSTED should be clear to light yellow in color and free of visible particles. Do not use if the liquid is cloudy or if visible particles are present. You may notice an air bubble, this is normal.

16.2 Storage and Handling

Do Not refrigerate or freeze. Use at room temperature.

- Store at controlled room temperature, 20°C to 25°C (68°F - 77°F); excursions permitted to 15°C to 30°C (59°F to 86°F).
- Protect from light (keep in carton until time of use).

17 PATIENT COUNSELING INFORMATION

Advise the patient to read the FDA-approved patient labeling (Medication Guide and Instructions for Use).

Venous Thromboembolism

- Inform patients that XYOSTED can cause venous thromboembolism. Advise patients of the signs and symptoms of venous thromboembolism, which may include the following: lower limb pain, edema, or erythema; and dyspnea or chest pain. Advise patients to promptly report the signs and symptoms of venous thromboembolism, discontinue use of XYOSTED, and seek urgent medical care.

Increased Blood Pressure and Risk for Major Adverse Cardiovascular Events (MACE)

- Inform patients that XYOSTED can increase BP which can increase cardiovascular risk over time.
- Instruct patients about the importance of monitoring BP periodically while on XYOSTED. If BP increases while on XYOSTED, antihypertensive medications may need to be started, added, or adjusted to control BP, or XYOSTED may need to be discontinued.

Other Adverse Reactions
Inform patients that treatment with androgens may lead to adverse reactions which include:

- Changes in urinary habits related to effects on prostate size, such as increased urination at night, hesitancy, urinary frequency, urinary urgency, having a urine accident, or being unable to pass urine or weak urine flow.
- Breathing disturbances that may reflect obstructive sleep apnea, including those associated with sleep or excessive daytime sleepiness.
- Too frequent or persistent erections of the penis.
- Ankle swelling that may reflect peripheral edema.
- Red blood cell count increase, PSA increase, injection site bruising, injection site bleeding.
  Instruct patients to report any changes in their state of health, such as changes in urinary habits, breathing, sleep, and mood, including new onset or worsening of depression, or suicidal ideation.

Keep XYOSTED out of the reach of children

For more information call: 1-844-XYOSTED (1-844-996-7833) or visit www.XYOSTED.com

Manufactured For: Antares Pharma, Inc. Ewing, NJ 08628

XYOSTED and the XYOSTED logo are trademarks of Antares Pharma, Inc. All rights reserved.

©2025 Antares Pharma, Inc. All rights reserved

MEDICATION GUIDE

XYOSTED® (ZYE-oh-sted)

(testosterone enanthate) injection, for subcutaneous use CIII

What is XYOSTED?

XYOSTED is a prescription medicine that contains testosterone. XYOSTED is used to treat adult men who have low or no testosterone due to certain medical conditions.

It is not known if XYOSTED is safe and effective in children younger than 18 years old. Improper use of XYOSTED may affect bone growth in children.

It is not known if XYOSTED is safe or effective to treat men who have low testosterone due to aging.

XYOSTED is a controlled substance (CIII) because it contains testosterone that can be a target for people who abuse prescription medicines. Keep your XYOSTED in a safe place to protect it. Never give your XYOSTED to anyone else, even if they have the same symptoms you have. Selling or giving away this medicine may harm others and it is against the law.

XYOSTED is not meant for use by women.

Do not take XYOSTED if you:

- are a man who has breast cancer.
- have or might have prostate cancer.
- are a woman who is pregnant. XYOSTED may harm your unborn baby.
- are allergic to XYOSTED or to any ingredients in XYOSTED including testosterone or sesame oil.

Before you use XYOSTED, tell your healthcare provider about all your medical conditions, including, if you:

- have high blood pressure or are being treated for high blood pressure.
- have heart problems.
- have high red blood cell count (hematocrit) or high hemoglobin laboratory value.
- have urinary problems due to an enlarged prostate.
- have kidney or liver problems.
- have a history of mental health illness including suicidal thoughts or actions, depression, anxiety or mood disorder.
- have problems breathing while you sleep (sleep apnea).

Tell your healthcare provider about all the medicines you take, including prescription and nonprescription medicines, vitamins, and herbal supplements.

Using XYOSTED with other medicines can affect each other. Especially, tell your healthcare provider if you take:

- insulin
- medicines that decrease blood clotting (blood thinners)
- corticosteroids
- medicines for pain and cold.

Know the medicines you take. Ask your healthcare provider or pharmacist for a list of all your medicines if you are not sure. Keep a list of them and show it to your healthcare provider and pharmacist when you get a new medicine.

How should I use XYOSTED?

- See the detailed Instructions for Use for information about how to use XYOSTED.
- Use XYOSTED exactly as your healthcare provider tells you to take it.
- Your healthcare provider will show you or your caregiver how to inject XYOSTED. You should not inject XYOSTED until you have been trained on the proper way to use it.

What are the possible side effects of XYOSTED?

XYOSTED can cause serious side effects including:

- Increase in red blood cell count (hematocrit) or hemoglobin.
  - XYOSTED increases red blood cell counts in some patients. High red blood cell counts increase the risk of clots, strokes, and heart attacks.
  - You may need to stop XYOSTED if your red blood cell count increases.
  - Your healthcare provider should check your red blood cell count and hemoglobin while you use XYOSTED.

- If you already have an enlarged prostate, your signs and symptoms may get worse while using XYOSTED. This can include:
  - increased urination at night
  - trouble starting your urine stream
  - having to pass urine many times during the day
  - having an urge that you have to go to the bathroom right away
  - having a urine accident
  - being unable to pass urine or weak urine flow

- Increased risk of prostate cancer. Your healthcare provider should check you for prostate cancer or any other prostate problems before you start and while you use XYOSTED.
- Blood clots in the legs or lungs. Signs and symptoms of a blood clot in your leg can include leg pain, swelling or redness. Signs and symptoms of a blood clot in your lungs can include difficulty breathing or chest pain.
- Increase in blood pressure. XYOSTED can increase your blood pressure. Increases in blood pressure can increase the risk of heart attack or stroke over time. Your risk may be greater if you have already had a heart attack or stroke or if you have other risk factors for heart attack or stroke. If your blood pressure increases while on XYOSTED, blood pressure medicines may need to be started. If you are taking blood pressure medicines, new blood pressure medicines may need to be added or your current blood pressure medicines may need to be adjusted to control your blood pressure. If your blood pressure cannot be controlled, XYOSTED may need to be stopped. Your healthcare provider will monitor your blood pressure while you are being treated with XYOSTED.
- Abuse. Testosterone can be abused, when taken at higher than prescribed doses and when used with other anabolic androgenic steroids. Abuse can cause serious heart and psychological side effects. Your healthcare provider should check you for signs of abuse before and during treatment with XYOSTED.
- In large doses XYOSTED may lower your sperm count.
- Liver problems. Symptoms of liver problems may include:
  - nausea or vomiting
  - yellowing of your skin or whites of your eyes
  - dark urine
  - pain on the right side of your stomach area (abdominal pain)

- Swelling of your ankles, feet, or body, with or without heart failure.
- Enlarged or painful breasts.
- Problems breathing while you sleep (sleep apnea).
- Change in mood. Talk to your healthcare provide if you have changes in mood or behavior including, new or worsening depression, or suicidal thoughts.

Call your healthcare provider right away if you have any of the serious side effects listed above.

The most common side effects of XYOSTED include:

- red blood cell count increase
- prostatic specific antigen (PSA) increase (a test used to screen for prostate cancer)
- high blood pressure
- injection site reactions including:
  - bruising
  - bleeding
  - redness
  - hardness

Other side effects include more erections than are normal for you or erections that last a long time.

Tell your healthcare provider if you have any side effect that bothers you or that does not go away.

These are not all the possible side effects of XYOSTED. For more information, ask your healthcare provider or pharmacist. Call your doctor for medical advice about side effects. You may report side effects to FDA at 1-800-FDA-1088.

How should I store XYOSTED?

Do not refrigerate or freeze. Use at room temperature.

Store at controlled room temperature, 68°F to 77°F (20°C to 25°C). Protect from light (keep in carton until time of use). Discard unused portion.

Keep XYOSTED and all medicines out of the reach of children.

General information about the safe and effective use of XYOSTED.

Medicines are sometimes prescribed for purposes other than those listed in a Medication Guide. Do not use XYOSTED for a condition for which it was not prescribed. Do not give XYOSTED to other people, even they have the same symptoms that you have. It may harm them. You can ask your pharmacist or healthcare provider for information about XYOSTED that is written for health professionals.

What are the ingredients in XYOSTED?

Active ingredient: testosterone enanthate

Inactive ingredients: sesame oil

Manufactured For:
Antares Pharma, Inc. Ewing, NJ 08628 XYOSTED and the XYOSTED logo are trademarks of Antares Pharma, Inc. All rights reserved. ©2025 Antares Pharma, Inc. All rights reserved

For more information, go to www.XYOSTED.com or call 1-844-XYOSTED (1-844-996-7833).

This Medication Guide has been approved by the U.S. Food and Drug Administration.
For controlled substances, Antares Pharma, Inc. will provide a one-time replacement medication to the patient if the original product is damaged or is unusable due to unforeseen circumstances.

Issued: 07/2025

Instructions for Use

XYOSTED®
Testosterone Enanthate Injection USP CIII

Single-dose auto-injector.
For a single subcutaneous administration.
Administer one device weekly.

Read this Instructions for Use before you start using XYOSTED (ZYE-oh-sted) and each time you get a refill. There may be new information. This leaflet does not take the place of talking with your healthcare provider about your medical condition or treatment.

Important Information about XYOSTED:

- Use XYOSTED exactly as your healthcare provider tells you to take it.
- Inject XYOSTED only 1 time each week. Do not use XYOSTED every day.
- Your healthcare provider will show you or your caregiver how to inject XYOSTED. You should not inject XYOSTED until you have been trained on the proper way to use it.
- Check XYOSTED before you inject it. XYOSTED should be clear to light yellow in color and should be free of visible particles.
- Do not use if the liquid is cloudy or if visible particles are present. You may see air bubble(s), this is normal.
- Do not use XYOSTED if the safety seal is broken or if the Auto-Injector appears broken, damaged or changed in any way.
- XYOSTED should be injected in the stomach (abdomen) area after cleaning the skin.
- Do not inject XYOSTED within 2 inches of the belly button (navel).
- Do not inject XYOSTED in any other areas of the body.
- Do not inject XYOSTED in areas where the skin is tender, bruised, red, scaly, hard, or has scars or stretch marks.
- Discard unused portion.

If you are not sure if XYOSTED was injected, or if you have a hard time giving the injection, do not inject another dose. Call your pharmacist or healthcare provider right away.

If you need help or instructions, call:
1-844-996-7833

- Carefully read all steps before beginning injection.
- Injection process must be completed without interruption.

Supplies You Will Need

- 1 XYOSTED Auto-Injector
- 1 alcohol swab
- 1 cotton ball or gauze

Storage Conditions

- Do not refrigerate or freeze.
- Protect from light.
- Use at room temperature.
- Store at 68° - 77° F (20° - 25° C).
- Keep XYOSTED and all medicines away from children.

Inspect Auto-Injector

- Do not remove Cap until ready to inject.
- Inspect Auto-Injector for any visible damage. Do not use if it appears damaged or broken.
- Check the expiration date. Do not use if the expiration date has passed.
- Inspect the medicine through the Viewing Window; it should be clear to light yellow and free of visible particles (see Figure 2).

Do not use if the medicine is cloudy or if visible particles are present. You may notice an air bubble, this is normal.

Select & Prep Injection Site

Wash your hands with soap and water.
Wipe the abdomen injection site with an alcohol swab.

Allow the site to dry on its own.
Do not fan or blow on the injection site.
Do not touch the site again before injecting.

Only use the left or right side of the abdomen (belly) for injection sites.
Do not use the area within 2 inches around your navel (belly button).
See Figure 3.

Do not use in areas where the skin is tender, bruised, red, scaly, or hard. Avoid areas with scars, tattoos, or stretch marks.

Administering Injection

1. Remove Cap

Twist the Cap to remove (this will also break the red safety seal). See Figure 4.

After the Cap is removed, a few drops of liquid may appear, this is normal.
The Auto-Injector should be used or discarded after the Cap is removed.
Do not re-Cap for later use.

Do not touch the Needle End of the Auto-Injector with your hand or fingers after the Cap is removed, doing so can cause injection and injury to your hands.

2. Position Auto-Injector

Gently squeeze the abdomen injection site to create a raised area and hold that area firmly until after the injection is complete (see Figure 5).

Place the Needle End of the Auto-Injector on the abdomen injection site.

Keep the Auto-Injector straight at a 90 degree angle to the abdomen injection site. (see Figure 6).

3. Inject & Hold Down

Firmly push the Auto-Injector down on the abdomen site and continue to hold down after you hear the “CLICK” (see Figure 7).

While holding the XYOSTED Auto-Injector down, slowly count from 1 to 10 to allow all of the medicine to be delivered (see Figure 8).

Keep holding the XYOSTED Auto-Injector down for a total of 10 seconds even if your injection is complete and the viewing window turns orange sooner.

It is normal if there is slight bleeding from the site after injection. If this occurs, hold a cotton ball or gauze on the area for a few seconds. Do not rub the area.

4. Inspect Viewing Window

After injecting, inspect the Viewing Window. It should be orange, confirming the dose was administered (see Figure 9).

If the Viewing Window is not orange:

- Do not use another Auto-Injector.
- Do not attempt another injection.
- Call your healthcare provider or 1-844-996-7833 for assistance.

Disposal After Injection

After completing your injection, dispose of the XYOSTED Auto-Injector and Cap in an FDA-cleared sharps disposal container immediately after use.

Do not dispose of the XYOSTED Auto-Injector in your household trash.

If you do not have an FDA-cleared sharps disposal container, you may use a household container that is:

- made of a heavy-duty plastic
- can be closed with a tight-fitting, puncture-resistant lid, without sharps being able to come out
- upright and stable during use
- leak-resistant
- properly labeled to warn of hazardous waste inside the container

When your sharps disposal container is almost full, you will need to follow your community guidelines for the proper way to dispose of your sharps disposal container. There may be state or local laws about how you should throw away used needles and syringes. For more information about safe sharps disposal in the state that you live in, go to the FDA’s website at: http://www.fda.gov/safesharpsdisposal.

Do not dispose of your used sharps disposal container in your household trash unless your community guidelines permit this. Do not recycle your used sharps disposal container.

This Instructions for Use has been approved by the U.S. Food and Drug Administration

LB-0118 V08

Manufactured for:
Antares Pharma, Inc.
Ewing, NJ 08628
03/2025

PRINCIPAL DISPLAY PANEL - 50 mg/0.5 mL Autoinjector

XYOSTED® (testosterone enathate injection, USP) CIII

50 mg/0.5 mL

NDC 54436-250-02

For subcutaneous injections only.
Single-dose autoinjector.
Discard after use. DO NOT reuse. Rx ONLY

PRINCIPAL DISPLAY PANEL - 75 mg/0.5 mL Autoinjector

XYOSTED® (testosterone enathate injection, USP) CIII

75 mg/0.5 mL

NDC 54436-275-02

For subcutaneous injections only.
Single-dose autoinjector.
Discard after use. DO NOT reuse. Rx ONLY

PRINCIPAL DISPLAY PANEL - 100 mg/0.5 mL Autoinjector

XYOSTED® (testosterone enathate injection, USP) CIII

100 mg/0.5 mL

NDC 54436-200-02

For subcutaneous injections only.
Single-dose autoinjector.
Discard after use. DO NOT reuse. Rx ONLY

PRINCIPAL DISPLAY PANEL - 50 mg/0.5 mL Carton of 4

XYOSTED® (testosterone enathate injection, USP)

NDC 54436-250-04

50 mg/0.5 mL

CIII

For subcutaneous injections only

Four Single-dose autoinjectors

Discard after use. DO NOT reuse.

Dispense the enclosed Medication Guide to each patient.

Rx ONLY

PRINCIPAL DISPLAY PANEL - 75 mg/0.5 mL Carton of 4

XYOSTED® (testosterone enathate injection, USP)

NDC 54436-275-04

75 mg/0.5 mL

CIII

For subcutaneous injections only

Four Single-dose autoinjectors

Discard after use. DO NOT reuse.

Dispense the enclosed Medication Guide to each patient.

Rx ONLY

PRINCIPAL DISPLAY PANEL - 100 mg/0.5 mL Carton of 4

XYOSTED® (testosterone enathate injection, USP)

NDC 54436-200-04

100 mg/0.5 mL

CIII

For subcutaneous injections only

Four Single-dose autoinjectors

Discard after use. DO NOT reuse.

Dispense the enclosed Medication Guide to each patient.

Rx ONLY